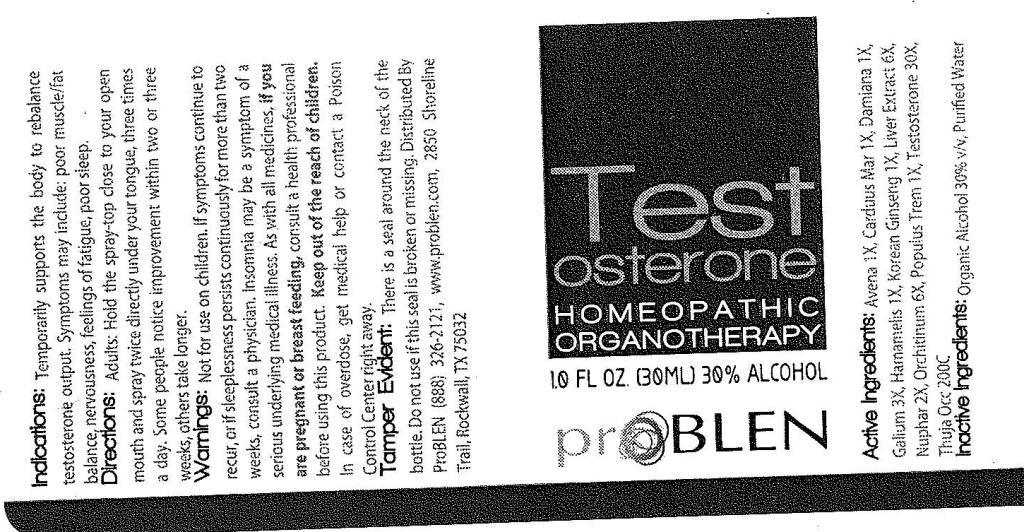 DRUG LABEL: Testosterone
NDC: 50845-0113 | Form: SPRAY
Manufacturer: Liddell Laboratories, Inc.
Category: homeopathic | Type: HUMAN OTC DRUG LABEL
Date: 20120223

ACTIVE INGREDIENTS: AVENA SATIVA FLOWERING TOP 1 [hp_X]/1 mL; SILYBUM MARIANUM SEED 1 [hp_X]/1 mL; TURNERA DIFFUSA LEAFY TWIG 1 [hp_X]/1 mL; GALIUM APARINE 3 [hp_X]/1 mL; HAMAMELIS VIRGINIANA ROOT BARK/STEM BARK 1 [hp_X]/1 mL; ASIAN GINSENG 1 [hp_X]/1 mL; POPULUS TREMULOIDES BARK 1 [hp_X]/1 mL; TESTOSTERONE 30 [hp_X]/1 mL; THUJA OCCIDENTALIS LEAFY TWIG 200 [hp_C]/1 mL; BEEF LIVER 6 [hp_X]/1 mL; NUPHAR LUTEUM ROOT 2 [hp_X]/1 mL; BOS TAURUS TESTICLE 6 [hp_X]/1 mL
INACTIVE INGREDIENTS: WATER; ALCOHOL

Testosterone

ACTIVE INGREDIENT

ACTIVE INGREDIENTS:Avena sativa 1X, Carduus marianus 1X, Damiana 1X, Galium aparine 3X, Hamamelis virginiana 1X, Hepar bovinum 6X, Korean ginseng 1X, Nuphar luteum 2X, Orchitinum bovinum 6X, Populus tremuloides 1X, Testosterone 30X, Thuja occidentalis 200C.

PURPOSE

INDICATIONS: Temporarily supports the body to rebalance testosterone output. Symptoms may include: poor muscle/fat balance, nervousness, feelings of fatigue, poor sleep.

WARNINGS

WARNINGS: Not for use on children. If symptoms continue to recur, or if sleeplessness persists continuously for more than two weeks, consult a physician. Insomnia may be a symptom of a serious underlying medical illness.

As with all medicines, if you are pregnant or breast feeding, consult a health professional before using this product.

Keep out of the reach of children. In case of overdose, get medical help or contact a Poison Control Center right away.

TAMPER EVIDENT: There is a seal around the neck of the bottle. Do not use if this seal is broken or missing.

DOSAGE AND ADMINISTRATION

DIRECTIONS: Adults: Hold the spray-top close to your open mouth and spray twice directly under your tongue, three times a day. Some people notice improvement within two or three weeks, others take longer.

INACTIVE INGREDIENT

INACTIVE INGREDIENTS: Organic alcohol 30% v/v, Purified water.

KEEP OUT OF REACH OF CHILDREN

KEEP OUT OF THE REACH OF CHILDREN. In case of overdose, get medical help or contact a Poison Control Center right away.

INDICATIONS AND USAGE

INDICATIONS: Temporarily supports the body to rebalance testosterone output. Symptoms may include: poor muscle/fat balance, nervousness, feelings of fatigue, poor sleep.

QUESTIONS

Distributed By ProBLEN

(888) 326-2121, www.problen.com

2850 Shoreline Trail

Rockwall, TX 75032

PACKAGE LABEL

Testosterone

HOMEOPATHIC

ORGANOTHERAPY

1 FL OZ (30ML)

proBLEN